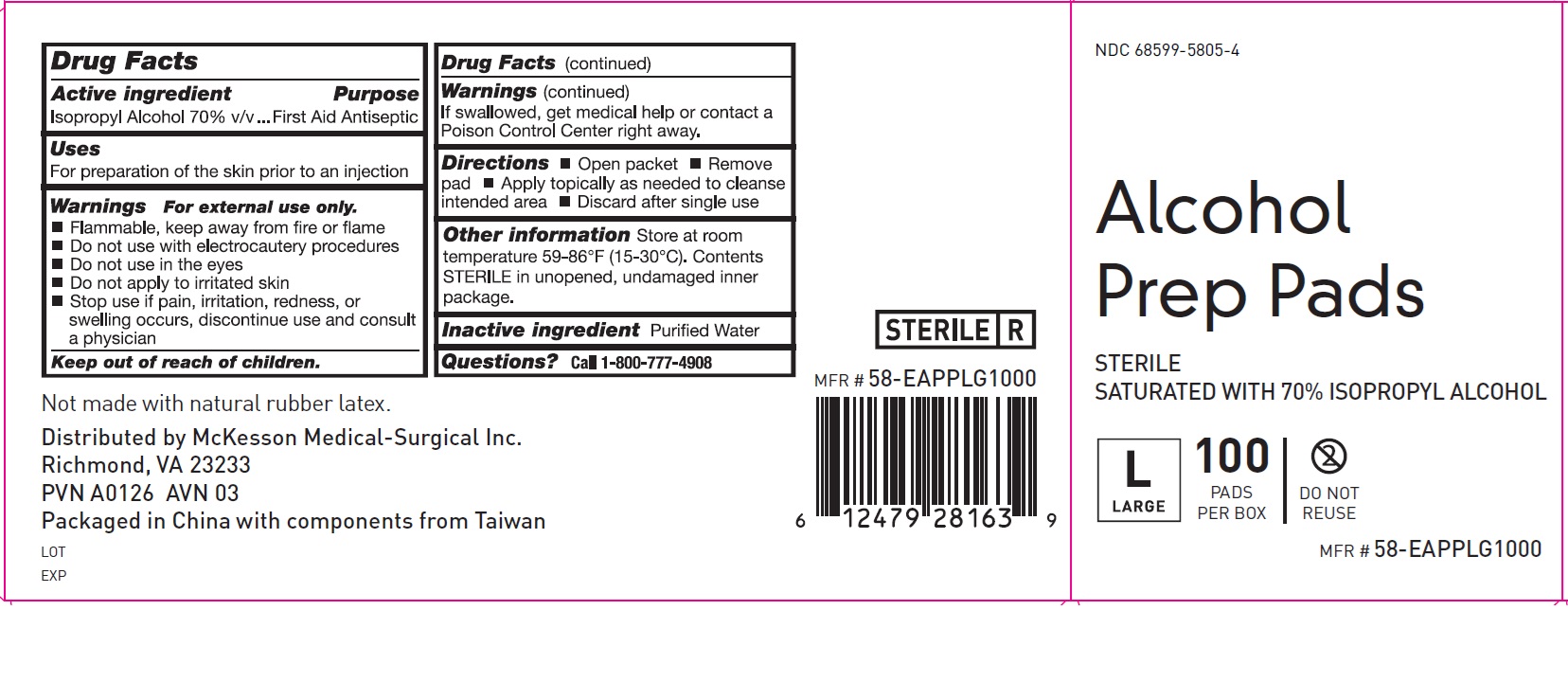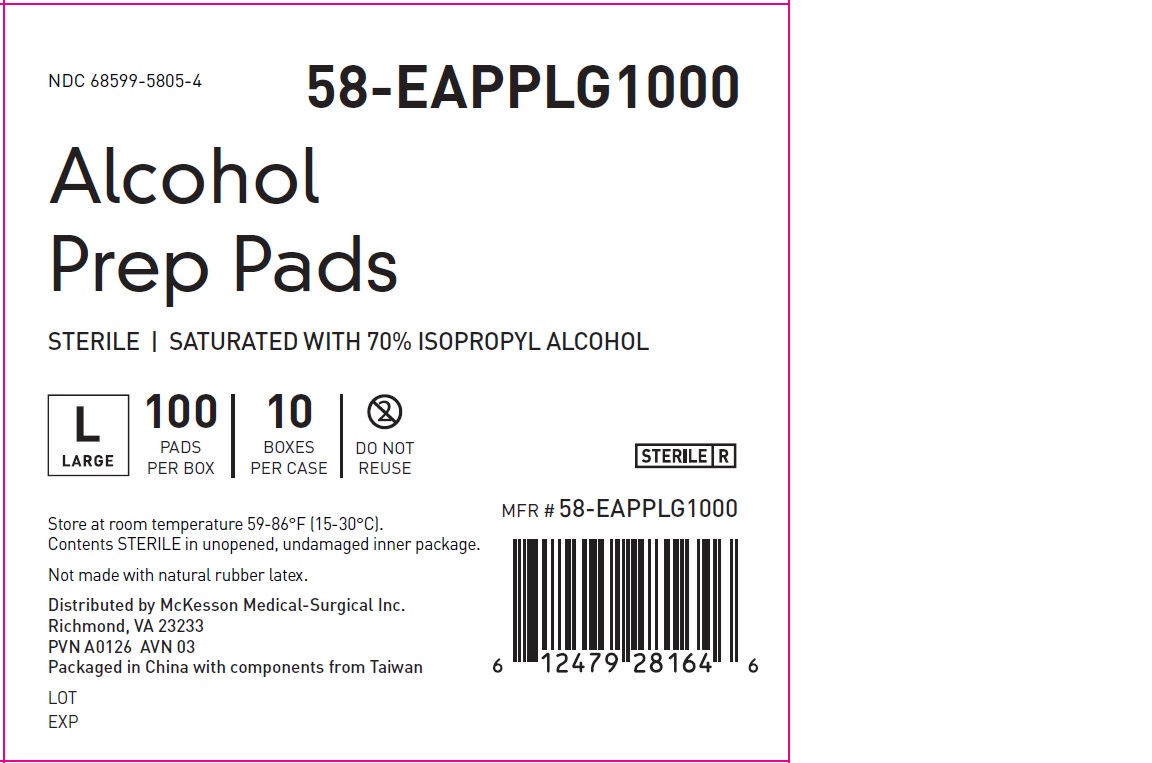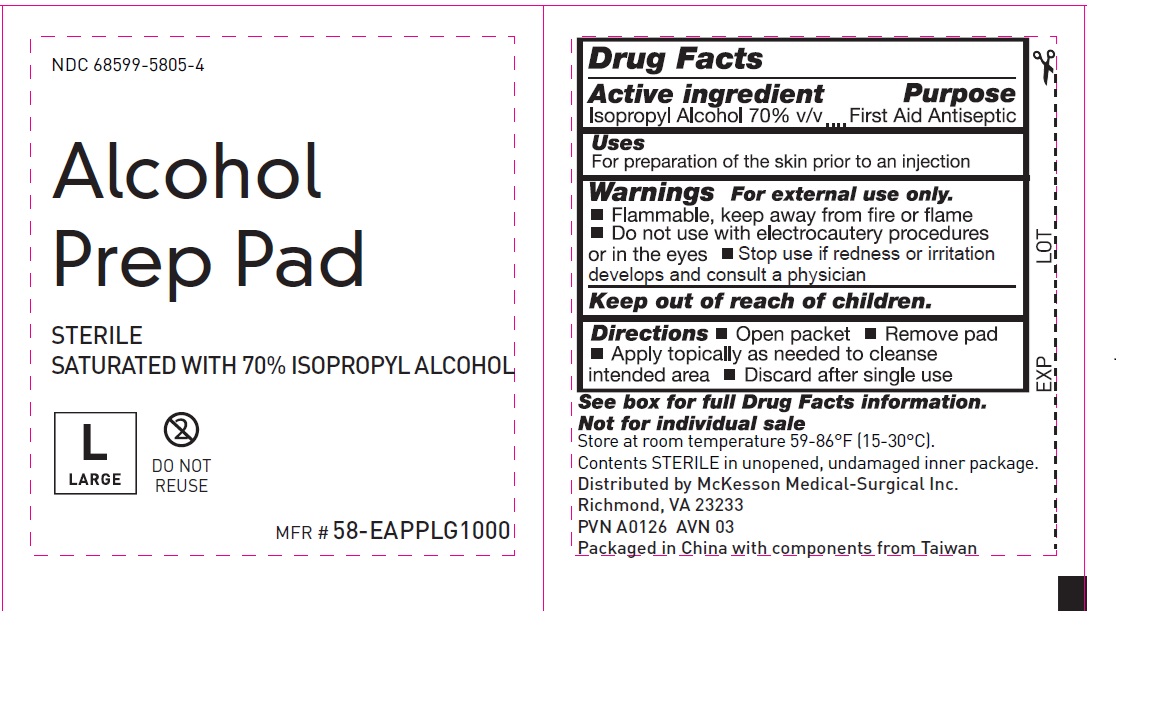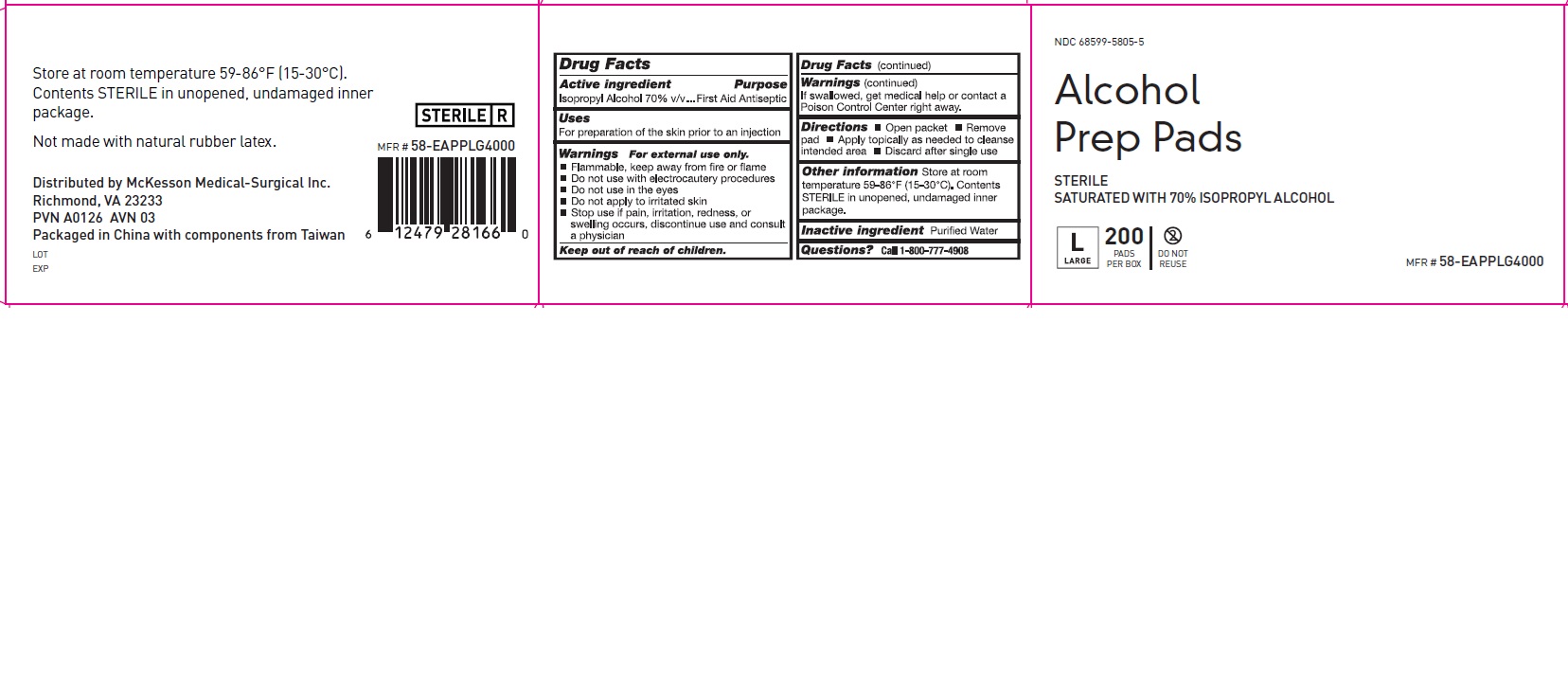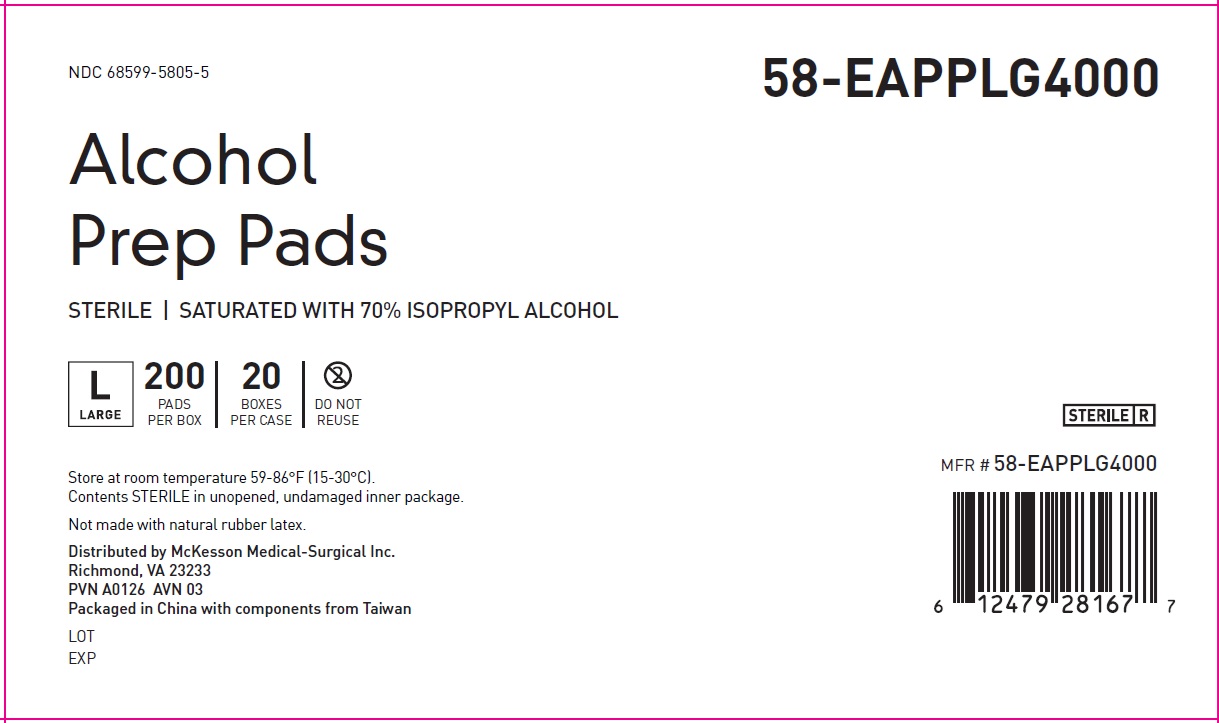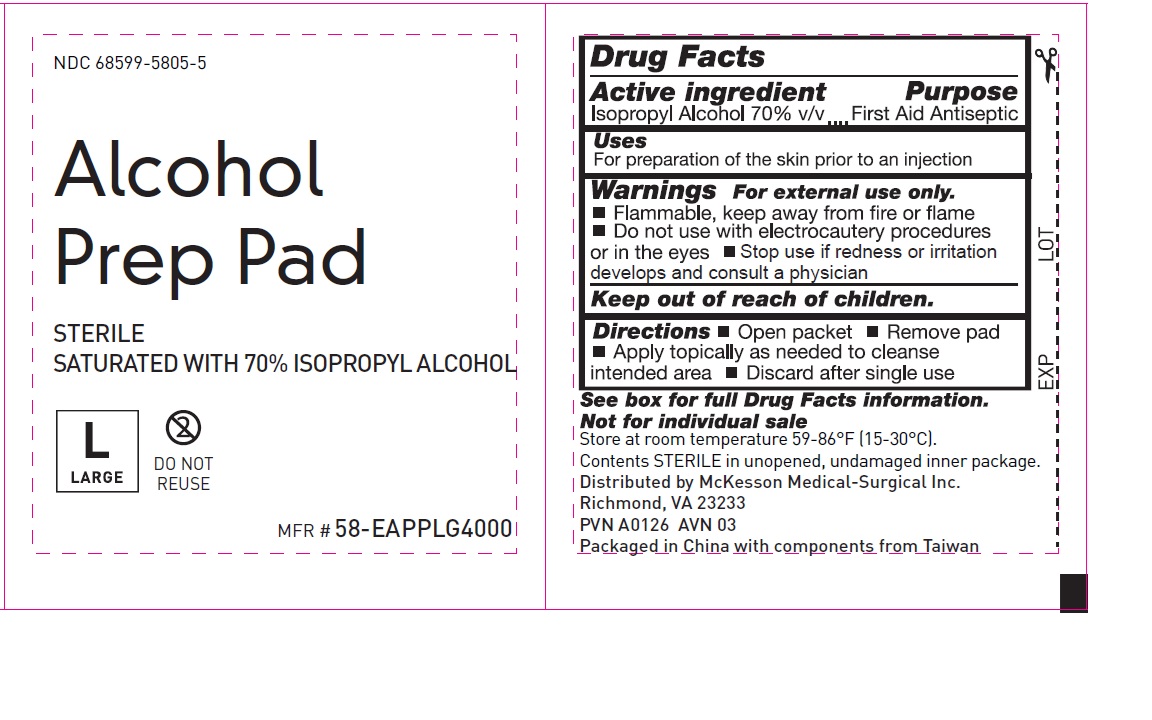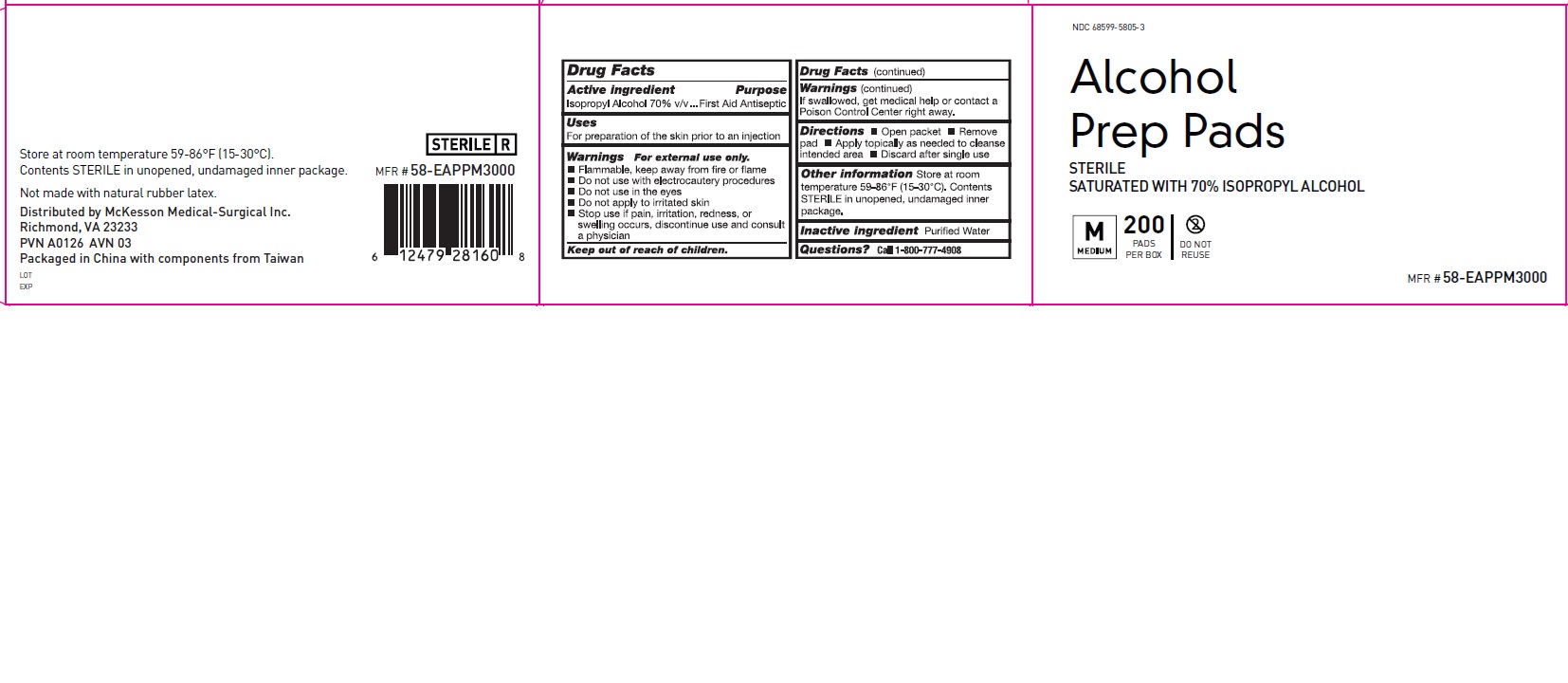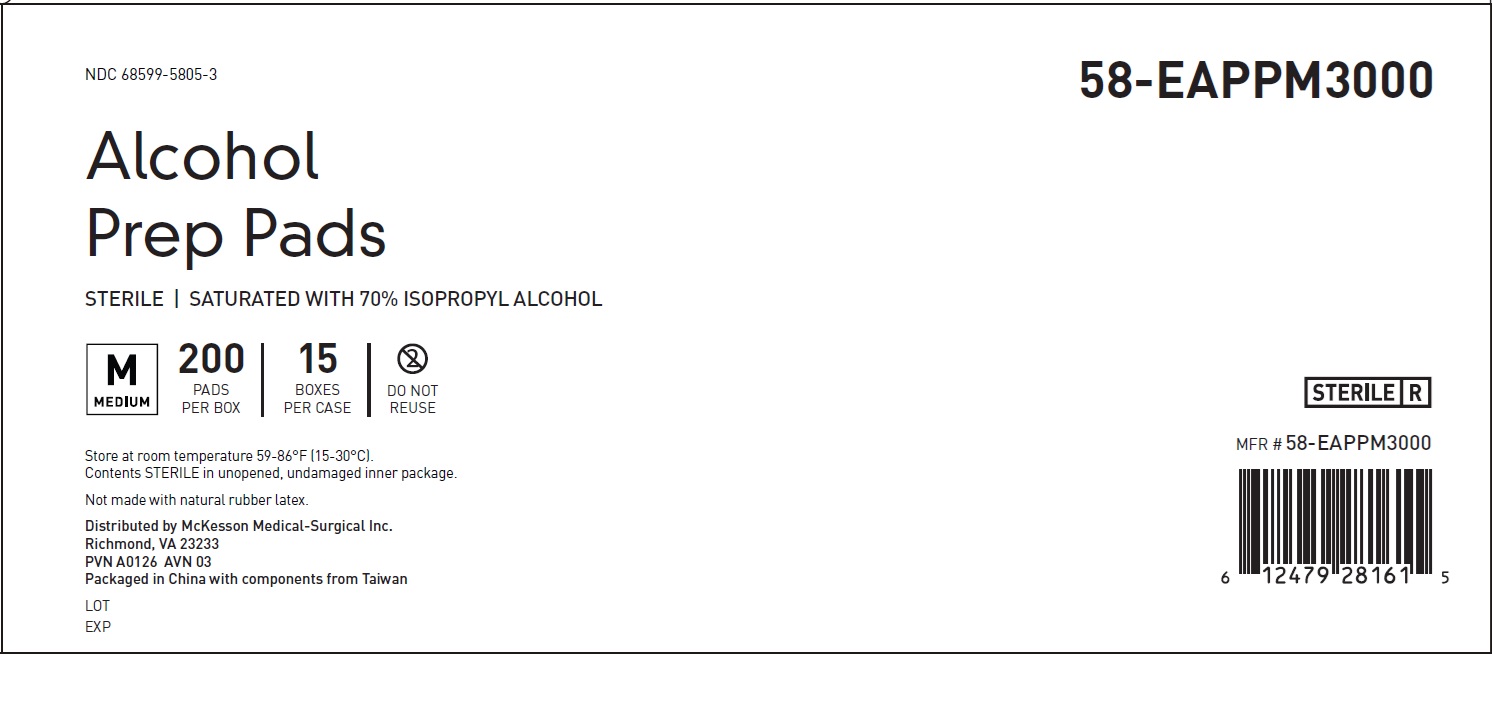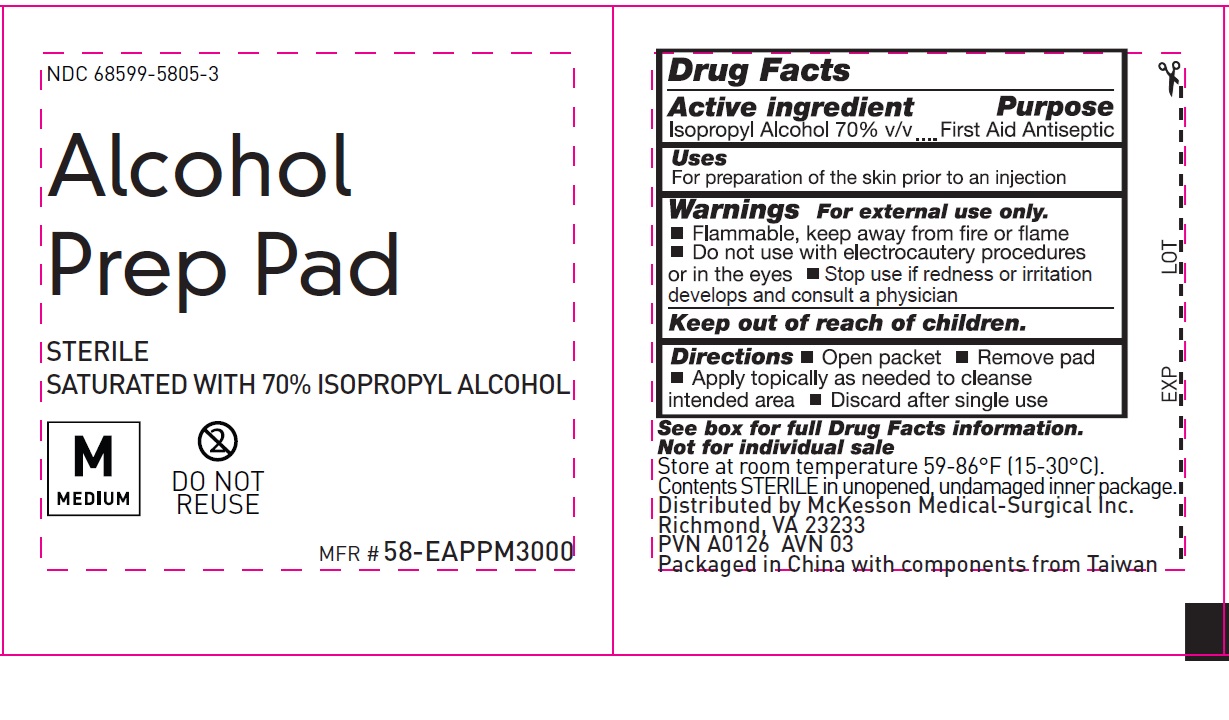 DRUG LABEL: Alcohol Prep Pad
NDC: 68599-5805 | Form: SWAB
Manufacturer: McKesson
Category: otc | Type: HUMAN OTC DRUG LABEL
Date: 20260212

ACTIVE INGREDIENTS: ISOPROPYL ALCOHOL 70 mL/100 mL
INACTIVE INGREDIENTS: WATER

Alcohol Prep Pads

Drug Facts

Active ingredient
Isopropyl Alcohol 70% v/v

Purpose
Antiseptic

Uses
For preparation of the skin prior to an Injection

Warnings

- For external use only
- Flammable, keep away from fire or flame
- Do not use with electrocautery procedures
- Do not use in the eyes
- Stop use if pain, irritation, redness, or swelling occurs, discontinue use and consult a physician
- If swallowed, get medical help or contact a poison Control Center right away

Keep out of reach of children.

Directions
Open packet - Remove pad - Apply topically as needed to cleanse intended area - Discard after single use

Other information
Store at room temperature 59-68F (15-30C). Contents STERILE in unopened, undamaged inner package.

Inactive ingredient
Purified water

Questions?Call 1-800-777-4908

PACKAGE LABEL

NDC 68599-5805-5

Alcohol Prep Pad

STERILE
SATURATED WITH 70% ISOPROPYL ALCOHOL

Large 1.75 in x 3 in (4.4 cm x 7.6 cm)

MFR # 58-EAPPLG4000

PACKAGE LABEL

NDC 68599-5805-4

Alcohol Prep Pad

STERILE
SATURATED WITH 70% ISOPROPYL ALCOHOL

Large 1.75 in x 3 in (4.4 cm x 7.6 cm)

MFR # 58-EAPPLG1000

PACKAGE LABEL

NDC 68599-5805-3

Alcohol Prep Pad

STERILE
SATURATED WITH 70% ISOPROPYL ALCOHOL

Medium 1.2 in x 2.4 in (3 cm x 6.1 cm)

MFR # 58-EAPPM3000